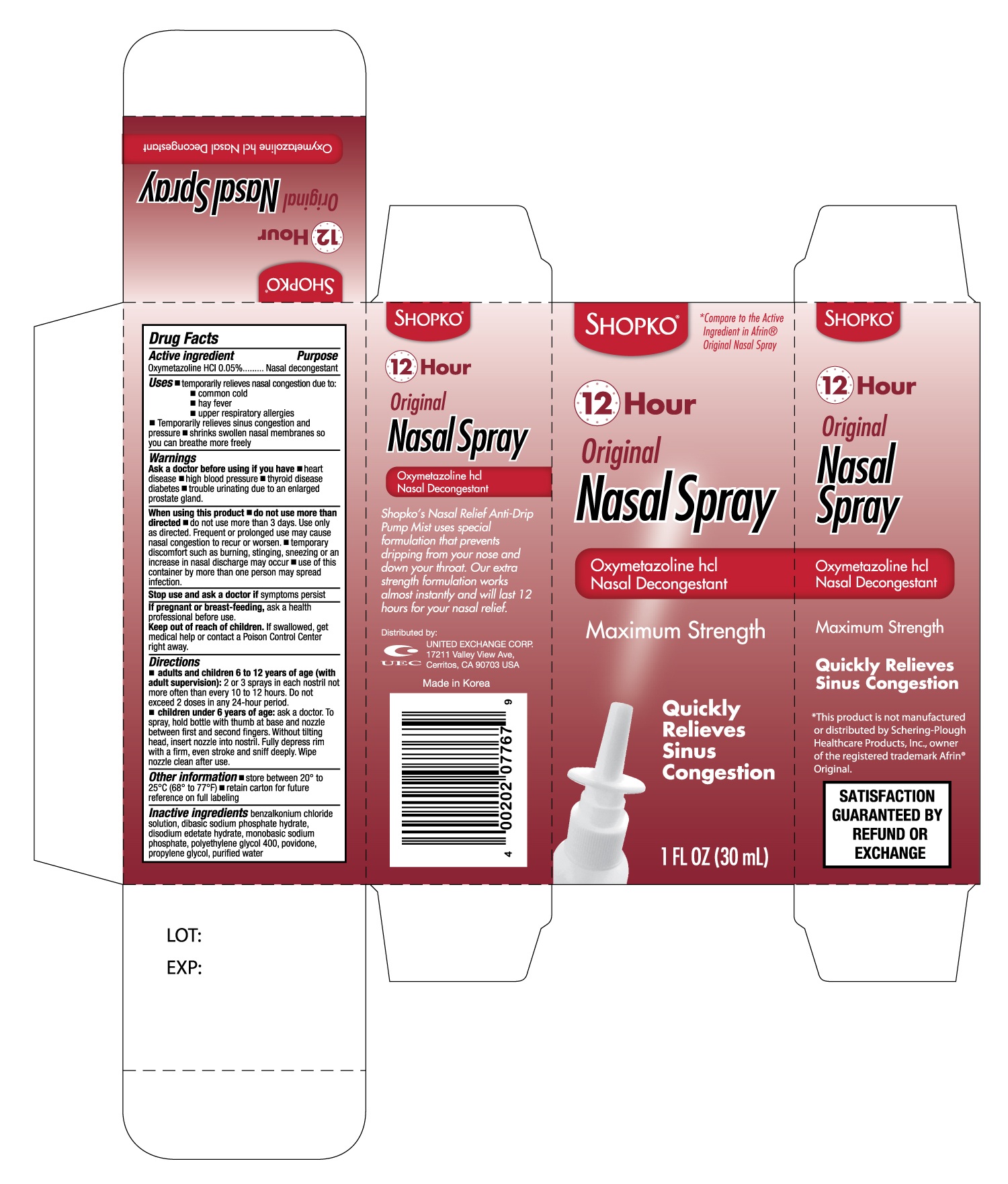 DRUG LABEL: SHOPKO ORIGINAL NASAL
NDC: 65923-077 | Form: SPRAY
Manufacturer: UNITED EXCHANGE CORP.
Category: otc | Type: HUMAN OTC DRUG LABEL
Date: 20120301

ACTIVE INGREDIENTS: OXYMETAZOLINE HYDROCHLORIDE 0.05 g/100 mL
INACTIVE INGREDIENTS: BENZALKONIUM CHLORIDE; POLYETHYLENE GLYCOL 400; POVIDONE; PROPYLENE GLYCOL; WATER

Drug Facts

Active Ingredient Purpose

Oxymetazoline hydrochloride 0.05% ......................................Nasal decongestant

Uses

- temporarily relieves nasal congestion due to
- common cold
- hay fever
- upper respiratory allergies
- sinusitis
- shrinks swollen nasal membranes so you can breathe more freely

Warnings

For external use only

Ask a doctor before use if you have

- heart disease
- high blood pressure
- thyroid disease
- diabetes
- trouble urinating due to an enlarged prostate gland

When using this product

- do not use more than directed
- do not use more than 3 days. Use only as directed. Frequent or prolonged use may cause nasal congestion to recur or worsen
- temporary discomfort such as burning, stinging, sneezing or an increase in nasal discharge may occur
- use of this container by more than one person may spread infection

Stop use and ask a doctor if symptoms persist

PREGNANCY OR BREAST FEEDING

If pregnant or breast-feeding, ask a health professional before use.

Keep out of reach of children. If swallowed, get medical help or contact a Poison Control Center right away.

Directions

- adults and children 6 to 12 years of age (with adult supervision) 2 or 3 sprays in each nostril not more often than every 10 to 12 hours. Do not exceed 2 doses in any 24-hour period.
- children under 6 years of age: ask a doctor.
- To spray, hold bottle with thumb at base and nozzle between first and second fingers. Without tilting head, insert nozzle into nostril Fully depress rim with a firm, even stroke and sniff deeply. Wipe nozzle clean after use.

Other information

- store between 15o and 25oC (59o and 77oF)
- retain carton for future reference on full labeling

INACTIVE INGREDIENT

Inactive ingredients: benzalkonium chloride solution, edetate disodium, polyethylene glycol, sodium phosphate dibasic, sodium phosphate monobasic, water

DOSAGE AND ADMINISTRATION

Distributed by:

UNITED EXCHANGE CORP.

17211 Valley View Ave.

Cerritos, CA 90703 USA

Made in Korea

PACKAGE LABEL

Enter section text here